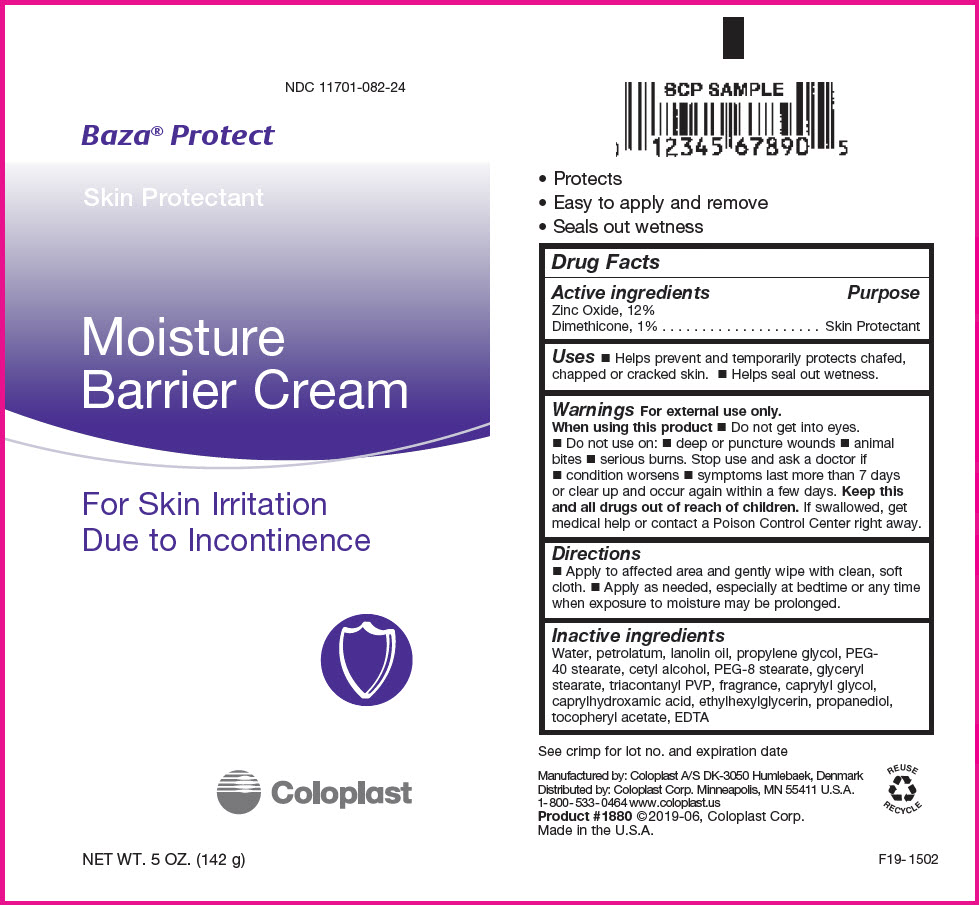 DRUG LABEL: Baza Protect
NDC: 11701-082 | Form: CREAM
Manufacturer: Coloplast Manufacturing US, LLC
Category: otc | Type: HUMAN OTC DRUG LABEL
Date: 20231222

ACTIVE INGREDIENTS: Zinc Oxide 120 mg/1 g; Dimethicone 10 mg/1 g
INACTIVE INGREDIENTS: Water; Petrolatum; Lanolin Oil; Propylene glycol; PEG-40 stearate; cetyl alcohol; PEG-8 stearate; Glyceryl Monostearate; Tricontanyl Povidone; Caprylyl glycol; Caprylhydroxamic acid; Ethylhexylglycerin; Propanediol; .alpha.-Tocopherol Acetate, DL-; EDETIC ACID

Baza® Protect

Drug Facts

Active ingredients

Zinc Oxide, 12%
Dimethicone, 1%

Purpose

Skin Protectant

Uses

- Helps prevent and temporarily protects chafed, chapped or cracked skin.
- Helps seal out wetness.

Warnings

For external use only.

When using this product

- Do not get into eyes.
- Do not use on:
  - deep or puncture wounds
  - animal bites
  - serious burns.

Stop use and ask a doctor if

- condition worsens
- symptoms last more than 7 days or clear up and occur again within a few days.

KEEP OUT OF REACH OF CHILDREN

Keep this and all drugs out of reach of children. If swallowed, get medical help or contact a Poison Control Center right away.

Directions

- Apply to affected area and gently wipe with clean, soft cloth.
- Apply as needed, especially at bedtime or any time when exposure to moisture may be prolonged.

Inactive ingredients

Water, petrolatum, lanolin oil, propylene glycol, PEG- 40 stearate, cetyl alcohol, PEG-8 stearate, glyceryl stearate, triacontanyl PVP, fragrance, caprylyl glycol, caprylhydroxamic acid, ethylhexylglycerin, propanediol, tocopheryl acetate, EDTA

Manufactured by: Coloplast A/S DK-3050 Humlebaek, Denmark

Distributed by: Coloplast Corp. Minneapolis, MN 55411 U.S.A.

PRINCIPAL DISPLAY PANEL - 142 g Tube Label

NDC 11701-082-24

Baza® Protect

Skin Protectant

Moisture
Barrier Cream

For Skin Irritation
Due to Incontinence

Coloplast

NET WT. 5 OZ. (142 g)